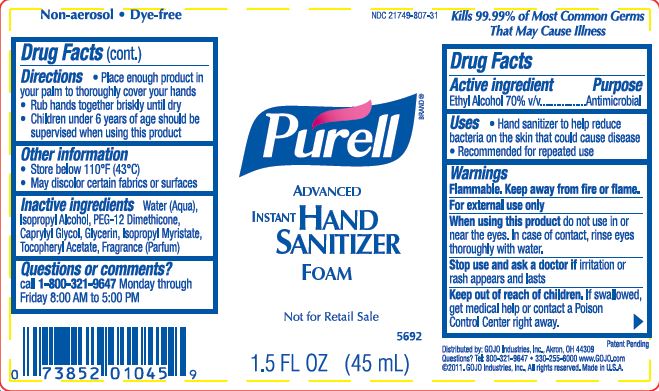 DRUG LABEL: PURELL Advanced Instant Hand Sanitizer
NDC: 21749-807 | Form: LIQUID
Manufacturer: GOJO Industries, Inc.
Category: otc | Type: HUMAN OTC DRUG LABEL
Date: 20260112

ACTIVE INGREDIENTS: ALCOHOL 0.7 mL/1 mL
INACTIVE INGREDIENTS: WATER; ISOPROPYL ALCOHOL; GLYCERIN; ISOPROPYL MYRISTATE; .ALPHA.-TOCOPHEROL ACETATE, D-; CAPRYLYL GLYCOL; PEG-12 DIMETHICONE (300 CST)

PURELL Advanced Instant Hand Sanitizer Foam

Active ingredient

Ethyl Alcohol 70%

Purpose

Antimicrobial

Use

Hand sanitizer to help reduce bacteria on the skin that could cause disease

Warnings

Flammable. Keep away from fire or flame.

For external use only.

When using this product, do not use in or near the eyes. In case of contact, rinse eyes thoroughly with water.

Stop use and ask a doctor ifirritation or rash appears and lasts

Keep out of reach of children.If swallowed, get medical help or contact a Poison Control Center right away.

Directions

Place enough product in your palm to thoroughly cover your hands.

Rub hands together briskly until dry.

Children under 6 years of age should be supervised when using this product.

Other information

Store below 110oF (43oC)

May discolor certain fabrics or surfaces

Inactive ingredients

Water (Aqua), Isopropyl Alcohol, PEG-12 Dimethicone, Caprylyl Glycol, Glycerin, Isopropyl Myristate, Tocopheryl Acetate, Fragrance (Parfum)